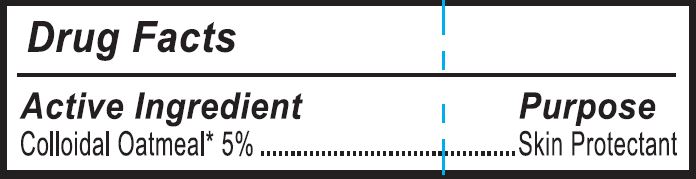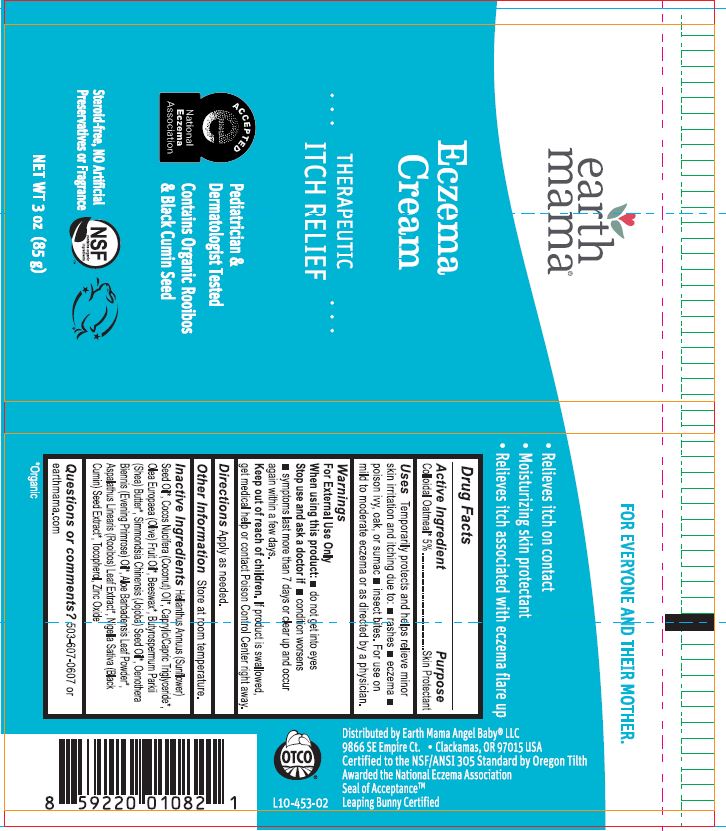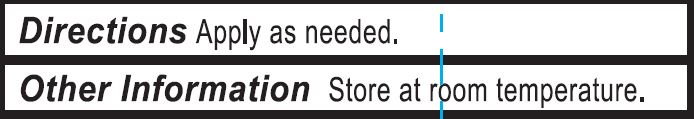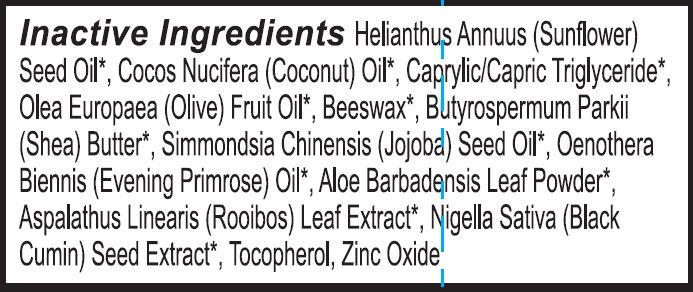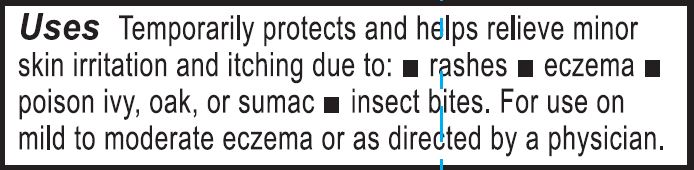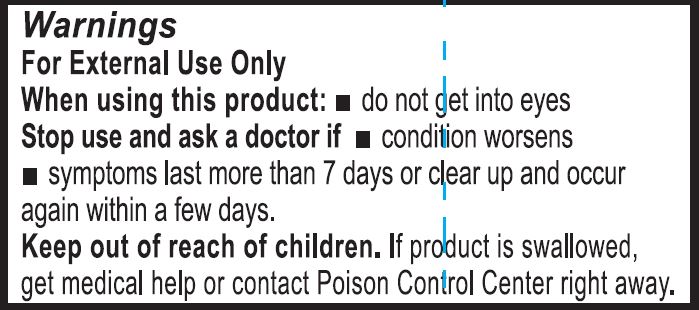 DRUG LABEL: Eczema Cream Therapeutic Itch Relief
NDC: 62932-229 | Form: OINTMENT
Manufacturer: Private Label Select Ltd CO
Category: otc | Type: HUMAN OTC DRUG LABEL
Date: 20220101

ACTIVE INGREDIENTS: OATMEAL 5 g/100 g
INACTIVE INGREDIENTS: WHITE WAX; ASPALATHUS LINEARIS WHOLE; EVENING PRIMROSE OIL; NIGELLA SATIVA SEED; OLIVE OIL; COCONUT OIL; SUNFLOWER OIL; MEDIUM-CHAIN TRIGLYCERIDES; JOJOBA OIL; SHEA BUTTER; .BETA.-TOCOPHEROL; .DELTA.-TOCOPHEROL; ZINC OXIDE; ALOE VERA LEAF; .GAMMA.-TOCOPHEROL; .ALPHA.-TOCOPHEROL, D-

Earth Mama Eczema Cream, Therapeutic Itch Relief